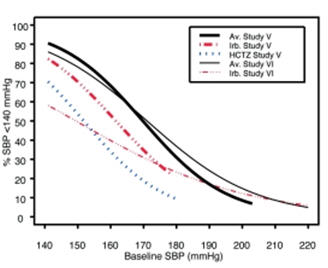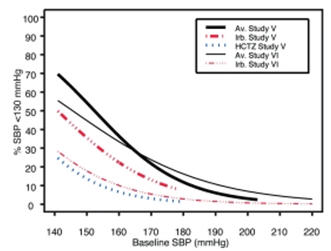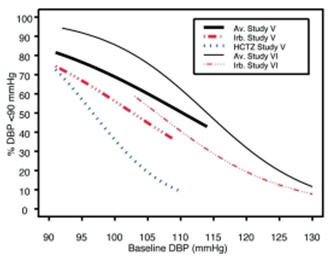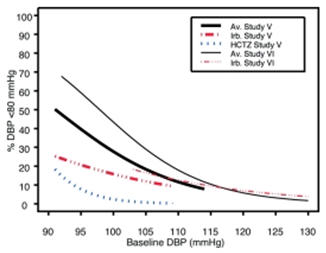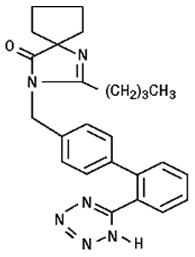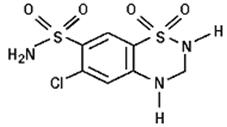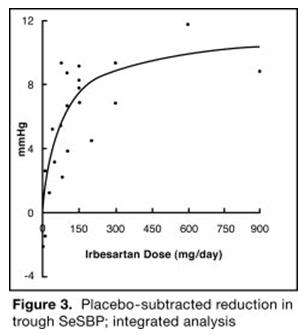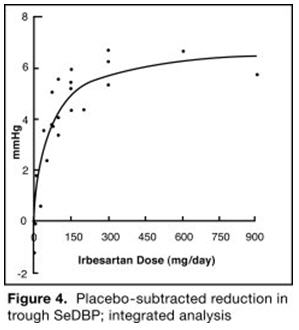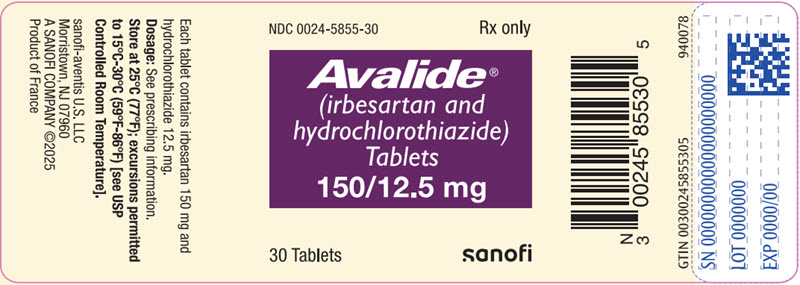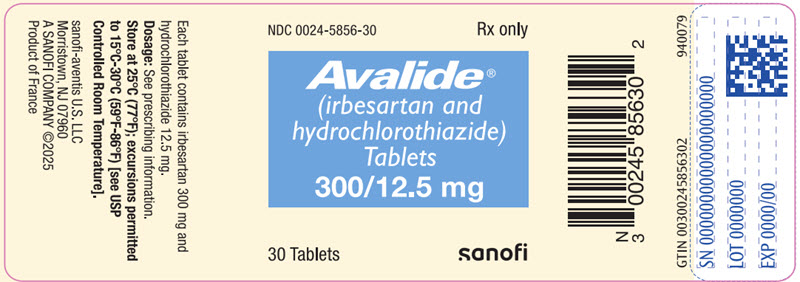 DRUG LABEL: Avalide
NDC: 0024-5855 | Form: TABLET, FILM COATED
Manufacturer: Sanofi-Aventis U.S. LLC
Category: prescription | Type: HUMAN PRESCRIPTION DRUG LABEL
Date: 20251007

ACTIVE INGREDIENTS: IRBESARTAN 150 mg/1 1; HYDROCHLOROTHIAZIDE 12.5 mg/1 1
INACTIVE INGREDIENTS: LACTOSE MONOHYDRATE; MICROCRYSTALLINE CELLULOSE; CROSCARMELLOSE SODIUM; HYPROMELLOSE, UNSPECIFIED; MAGNESIUM STEARATE; SILICON DIOXIDE; FERRIC OXIDE RED; FERRIC OXIDE YELLOW; POLYETHYLENE GLYCOL, UNSPECIFIED; TITANIUM DIOXIDE; CARNAUBA WAX

HIGHLIGHTS OF PRESCRIBING INFORMATION

These highlights do not include all the information needed to use AVALIDE safely and effectively. See full prescribing information for AVALIDE.
AVALIDE® (irbesartan and hydrochlorothiazide) tablets, for oral use
Initial U.S. Approval: 1997

WARNING: FETAL TOXICITY

See full prescribing information for complete boxed warning.

- When pregnancy is detected, discontinue AVALIDE as soon as possible. (5.1, 8.1)
- Drugs that act directly on the renin-angiotensin system can cause injury and death to the developing fetus. (5.1, 8.1)

1 INDICATIONS AND USAGE

AVALIDE is a combination of irbesartan, an angiotensin II receptor antagonist, and hydrochlorothiazide, a thiazide diuretic, indicated for hypertension:

- In patients not adequately controlled with monotherapy. (1)
- As initial therapy in patients likely to need multiple drugs to achieve their blood pressure goals. (1)

2 DOSAGE AND ADMINISTRATION

General Considerations

- Maximum effects within 2 to 4 weeks after dose change. (2.1)
- Renal impairment: Not recommended for patients with severe renal impairment (creatinine clearance <30 mL/min). (2.1, 5.8)

Hypertension

- Initiate with 150/12.5 mg. Titrate to 300/12.5 mg then 300/25 mg if needed. (2.2)
- Replacement therapy: May be substituted for titrated components. (2.3)

3 DOSAGE FORMS AND STRENGTHS

- 150 mg irbesartan/12.5 mg hydrochlorothiazide tablets (3)
- 300 mg irbesartan/12.5 mg hydrochlorothiazide tablets (3)

4 CONTRAINDICATIONS

- Hypersensitivity to any component of this product. (4)
- Anuria. (4)
- Hypersensitivity to sulfonamide-derived drugs. (4)
- Do not coadminister aliskiren with AVALIDE in patients with diabetes. (4)

5 WARNINGS AND PRECAUTIONS

- Hypotension: Correct volume depletion prior to administration. (5.2)
- Impaired renal function. (5.7)
- Thiazide diuretics may cause an exacerbation or activation of systemic lupus erythematosus. (5.4)
- Acute angle-closure glaucoma, acute myopia, and choroidal effusion. (5.8)

6 ADVERSE REACTIONS

- Most common adverse events (≥5% on AVALIDE and more often than on placebo) are dizziness, fatigue, and musculoskeletal pain. (6.1)

To report SUSPECTED ADVERSE REACTIONS, contact sanofi-aventis U.S. LLC at 1-800-633-1610 or FDA at 1-800-FDA-1088 or www.fda.gov/medwatch.

7 DRUG INTERACTIONS

- NSAIDs and selective COX-2 inhibitors: Can reduce diuretic, natriuretic of diuretic, may lead to increased risk of renal impairment and reduced antihypertensive effect. Monitor renal function periodically. (7)
- Dual blockade of the renin-angiotensin system: Increased risk of renal impairment, hypotension, and hyperkalemia. (7)
- Antidiabetic drugs: Dosage adjustment of antidiabetic may be required. (7)
- Cholestyramine and colestipol: Reduced absorption of thiazides. (7)
- Lithium: Increases in serum lithium concentrations and lithium toxicity. (7)
- Carbamazepine: Increased risk of hyponatremia. (7)

8 USE IN SPECIFIC POPULATIONS

- Lactation: Potential for adverse effects in infant. (8.2)

FULL PRESCRIBING INFORMATION

WARNING: FETAL TOXICITY

- When pregnancy is detected, discontinue AVALIDE as soon as possible [see Warnings and Precautions (5.1) and Use in Specific Populations (8.1)].
- Drugs that act directly on the renin-angiotensin system can cause injury and death to the developing fetus [see Warnings and Precautions (5.1) and Use in Specific Populations (8.1)].

1 INDICATIONS AND USAGE

AVALIDE® (irbesartan and hydrochlorothiazide) tablets are indicated for the treatment of hypertension.

AVALIDE may be used in patients whose blood pressure is not adequately controlled on monotherapy.

AVALIDE may also be used as initial therapy in patients who are likely to need multiple drugs to achieve their blood pressure goals.

The choice of AVALIDE as initial therapy for hypertension should be based on an assessment of potential benefits and risks.

Patients with stage 2 (moderate or severe) hypertension are at relatively high risk for cardiovascular events (such as strokes, heart attacks, and heart failure), kidney failure, and vision problems, so prompt treatment is clinically relevant. The decision to use a combination as initial therapy should be individualized and may be shaped by considerations such as the baseline blood pressure, the target goal, and the incremental likelihood of achieving goal with a combination compared with monotherapy.

Data from Studies V and VI [see Clinical Studies (14.2)] provide estimates of the probability of reaching a blood pressure goal with AVALIDE compared to irbesartan or hydrochlorothiazide (HCTZ) monotherapy. The relationship between baseline blood pressure and achievement of a SeSBP <140 or <130 mmHg or SeDBP <90 or <80 mmHg in patients treated with AVALIDE compared to patients treated with irbesartan or HCTZ monotherapy are shown in Figures 1a through 2b.

Figure 1a: Probability of Achieving SBP <140 mmHg in Patients from Initial Therapy Studies V (Week 8) and VI (Week 7) [For all probability curves, patients without blood pressure measurements at Week 7 (Study VI) and Week 8 (Study V) were counted as not reaching goal (intent-to-treat analysis).]

Figure 1b: Probability of Achieving SBP <130 mmHg in Patients from Initial Therapy Studies V (Week 8) and VI (Week 7)

Figure 2a: Probability of Achieving DBP <90 mmHg in Patients from Initial Therapy Studies V (Week 8) and VI (Week 7)

Figure 2b: Probability of Achieving DBP <80 mmHg in Patients from Initial Therapy Studies V (Week 8) and VI (Week 7)

The above graphs provide a rough approximation of the likelihood of reaching a targeted blood pressure goal (e.g., Week 8 sitting systolic blood pressure ≤140 mmHg) for the treatment groups. The curve of each treatment group in each study was estimated by logistic regression modeling from all available data of that treatment group. The estimated likelihood at the right tail of each curve is less reliable due to small numbers of subjects with high baseline blood pressures.

For example, a patient with a blood pressure of 180/105 mmHg has about a 25% likelihood of achieving a goal of <140 mmHg (systolic) and 50% likelihood of achieving <90 mmHg (diastolic) on irbesartan alone (and lower still likelihoods on HCTZ alone).

The likelihood of achieving these goals on AVALIDE rises to about 40% (systolic) or 70% (diastolic).

2 DOSAGE AND ADMINISTRATION

2.1 General Considerations

The side effects of irbesartan are generally rare and apparently independent of dose; those of hydrochlorothiazide are a mixture of dose-dependent (primarily hypokalemia) and dose-independent phenomena (e.g., pancreatitis), the former much more common than the latter. [See Adverse Reactions (6).]

Maximum antihypertensive effects are attained within 2 to 4 weeks after a change in dose.

AVALIDE may be administered with or without food.

AVALIDE may be administered with other antihypertensive agents.

Renal Impairment

The usual regimens of therapy with AVALIDE may be followed as long as the patient's creatinine clearance is >30 mL/min. In patients with more severe renal impairment, loop diuretics are preferred to thiazides, so AVALIDE is not recommended.

Hepatic Impairment

No dosage adjustment is necessary in patients with hepatic impairment.

2.2 Add-On Therapy

In patients not controlled on monotherapy with irbesartan or hydrochlorothiazide, the recommended doses of AVALIDE, in order of increasing mean effect, are (irbesartan and hydrochlorothiazide) 150/12.5 mg, 300/12.5 mg, and 300/25 mg. The largest incremental effect will likely be in the transition from monotherapy to 150/12.5 mg. [See Clinical Studies (14.2).]

2.3 Replacement Therapy

AVALIDE may be substituted for the titrated components.

2.4 Initial Therapy

The usual starting dose is AVALIDE 150/12.5 mg once daily. The dosage can be increased after 1 to 2 weeks of therapy to a maximum of 300/25 mg once daily as needed to control blood pressure [see Clinical Studies (14.2)]. AVALIDE is not recommended as initial therapy in patients with intravascular volume depletion [see Warnings and Precautions (5.2)].

3 DOSAGE FORMS AND STRENGTHS

AVALIDE® (irbesartan and hydrochlorothiazide) 150/12.5 mg and 300/12.5 mg film-coated tablets are peach, biconvex, and oval with a heart debossed on one side and "2875" or "2876" on the reverse side, respectively.

4 CONTRAINDICATIONS

- AVALIDE is contraindicated in patients who are hypersensitive to any component of this product.
- Because of the hydrochlorothiazide component, this product is contraindicated in patients with anuria or hypersensitivity to other sulfonamide-derived drugs.
- Do not coadminister aliskiren with AVALIDE in patients with diabetes [see Drug Interactions (7)].

5 WARNINGS AND PRECAUTIONS

5.1 Fetal Toxicity

AVALIDE can cause fetal harm when administered to a pregnant woman. Use of drugs that act on the renin-angiotensin system during the second and third trimesters of pregnancy reduces fetal renal function and increases fetal and neonatal morbidity and death. Resulting oligohydramnios can be associated with fetal lung hypoplasia and skeletal deformations. Potential neonatal adverse effects include skull hypoplasia, anuria, hypotension, renal failure, and death. When pregnancy is detected, discontinue AVALIDE as soon as possible [see Use in Specific Populations (8.1)].

Thiazides cross the placenta and use of thiazides during pregnancy is associated with a risk of fetal or neonatal jaundice, thrombocytopenia, and possibly other adverse reactions that have occurred in adults.

5.2 Hypotension in Volume or Salt-Depleted Patients

Excessive reduction of blood pressure was rarely seen in patients with uncomplicated hypertension treated with irbesartan alone (<0.1%) or with irbesartan and hydrochlorothiazide (approximately 1%). Initiation of antihypertensive therapy may cause symptomatic hypotension in patients with intravascular volume or sodium depletion, e.g., in patients treated vigorously with diuretics or in patients on dialysis. Such volume depletion should be corrected prior to administration of antihypertensive therapy.

If hypotension occurs, the patient should be placed in the supine position and, if necessary, given an intravenous infusion of normal saline. A transient hypotensive response is not a contraindication to further treatment, which usually can be continued without difficulty once the blood pressure has stabilized.

5.3 Hypersensitivity Reaction

Hydrochlorothiazide

Hypersensitivity reactions to hydrochlorothiazide may occur in patients with or without a history of allergy or bronchial asthma, but are more likely in patients with such a history.

5.4 Systemic Lupus Erythematosus

Hydrochlorothiazide

Thiazide diuretics have been reported to cause exacerbation or activation of systemic lupus erythematosus.

5.5 Electrolyte and Metabolic Imbalances

Irbesartan and Hydrochlorothiazide

In double-blind clinical trials of various doses of irbesartan and hydrochlorothiazide, the incidence of hypertensive patients who developed hypokalemia (serum potassium <3.5 mEq/L) was 7.5% versus 6.0% for placebo; the incidence of hyperkalemia (serum potassium >5.7 mEq/L) was <1.0% versus 1.7% for placebo. No patient discontinued due to increases or decreases in serum potassium. On average, the combination of irbesartan and hydrochlorothiazide had no effect on serum potassium. Higher doses of irbesartan ameliorated the hypokalemic response to hydrochlorothiazide.

Coadministration of AVALIDE with potassium-sparing diuretics, potassium supplements, potassium-containing salt substitutes or other drugs that raise serum potassium levels may result in hyperkalemia, sometimes severe. Monitor serum potassium in such patients.

Hydrochlorothiazide

Hydrochlorothiazide can cause hypokalemia and hyponatremia. Hypomagnesemia can result in hypokalemia which appears difficult to treat despite potassium repletion. Drugs that inhibit the renin-angiotensin system can cause hyperkalemia. Monitor serum electrolytes periodically.

Hyperuricemia may occur or frank gout may be precipitated in certain patients receiving thiazide therapy.

Hydrochlorothiazide may alter glucose tolerance and raise serum levels of cholesterol and triglycerides.

The antihypertensive effects of the drug may be enhanced in the post-sympathectomy patient.

Thiazides may decrease urinary calcium excretion. Thiazides may cause intermittent and slight elevation of serum calcium in the absence of known disorders of calcium metabolism. Marked hypercalcemia may be evidence of hidden hyperparathyroidism. Thiazides should be discontinued before carrying out tests for parathyroid function.

5.6 Hepatic Impairment

Hydrochlorothiazide

Thiazides should be used with caution in patients with impaired hepatic function or progressive liver disease since minor alterations of fluid and electrolyte balance may precipitate hepatic coma.

5.7 Impaired Renal Function

As a consequence of inhibiting the renin-angiotensin-aldosterone system, changes in renal function may be anticipated in susceptible individuals [see Drug Interactions (7)]. In patients whose renal function may depend on the activity of the renin-angiotensin-aldosterone system (e.g., patients with severe congestive heart failure), treatment with ACE inhibitors has been associated with oliguria and/or progressive azotemia and (rarely) with acute renal failure and/or death. Irbesartan would be expected to behave similarly. In studies of ACE inhibitors in patients with unilateral or bilateral renal artery stenosis, increases in serum creatinine or BUN have been reported. There has been no known use of irbesartan in patients with unilateral or bilateral renal artery stenosis, but a similar effect should be anticipated.

Thiazides should be used with caution in severe renal disease. In patients with renal disease, thiazides may precipitate azotemia. Cumulative effects of the drug may develop in patients with impaired renal function.

5.8 Acute Angle-Closure Glaucoma, Acute Myopia, and Choroidal Effusion

Hydrochlorothiazide

Hydrochlorothiazide, a sulfonamide, can cause an idiosyncratic reaction resulting in acute angle-closure glaucoma and elevated intraocular pressure with or without a noticeable acute myopic shift and/or choroidal effusions. Cases of acute angle-closure glaucoma have been reported with hydrochlorothiazide. Symptoms include acute onset of decreased visual acuity or ocular pain and typically occur within hours to weeks of drug initiation. Untreated acute angle-closure glaucoma may result in permanent vision loss. The primary treatment is to discontinue drug intake as rapidly as possible. Prompt medical or surgical treatments may need to be considered if the intraocular pressure remains uncontrolled. Risk factors for developing acute angle-closure glaucoma may include a history of sulfonamide or penicillin allergy.

6 ADVERSE REACTIONS

6.1 Clinical Trials Experience

Because clinical trials are conducted under widely varying conditions, adverse reaction rates observed in the clinical trials of a drug cannot be directly compared to rates in the clinical trials of another drug and may not reflect the rates observed in practice. The adverse reaction information from clinical trials does, however, provide a basis for identifying the adverse events that appear to be related to drug use and for approximating rates.

Irbesartan and Hydrochlorothiazide

AVALIDE tablets have been evaluated for safety in 1694 patients treated for essential hypertension in 6 clinical trials. In Studies I through IV with AVALIDE, no adverse events peculiar to this combination drug product have been observed. Adverse events have been limited to those that were reported previously with irbesartan or hydrochlorothiazide (HCTZ). The overall incidence of adverse events was similar with the combination and placebo. In general, treatment with AVALIDE was well tolerated. For the most part, adverse events have been mild and transient in nature and have not required discontinuation of therapy. In controlled clinical trials, discontinuation of AVALIDE therapy due to clinical adverse events was required in only 3.6%. This incidence was significantly less (p=0.023) than the 6.8% of patients treated with placebo who discontinued therapy.

In these double-blind controlled clinical trials, the following adverse events reported with AVALIDE occurred in ≥1% of patients, and more often on the irbesartan and hydrochlorothiazide combination than on placebo, regardless of drug relationship:

 | Irbesartan/HCTZ (n=898) (%) | Placebo (n=236) (%) | Irbesartan (n=400) (%) | HCTZ (n=380) (%)
Body as a Whole
Chest Pain | 2 | 1 | 2 | 2
Fatigue | 6 | 3 | 4 | 3
Influenza | 3 | 1 | 2 | 2
Cardiovascular
Edema | 3 | 3 | 2 | 2
Tachycardia | 1 | 0 | 1 | 1
Gastrointestinal
Abdominal Pain | 2 | 1 | 2 | 2
Dyspepsia/heartburn | 2 | 1 | 0 | 2
Nausea/vomiting | 3 | 0 | 2 | 2
Immunology
Allergy | 1 | 0 | 1 | 1
Musculoskeletal
Musculoskeletal Pain | 6 | 5 | 6 | 10
Nervous System
Dizziness | 8 | 4 | 6 | 5
Dizziness Orthostatic | 1 | 0 | 1 | 1
Renal/Genitourinary
Abnormality Urination | 2 | 1 | 1 | 2

The following adverse events were also reported at a rate of 1% or greater, but were as, or more, common in the placebo group: headache, sinus abnormality, cough, URI, pharyngitis, diarrhea, rhinitis, urinary tract infection, rash, anxiety/nervousness, and muscle cramp.

Adverse events occurred at about the same rates in men and women, older and younger patients, and black and non-black patients.

Adverse events in Studies V and VI were similar to those described above in Studies I through IV.

Irbesartan

Other adverse events that have been reported with irbesartan, without regard to causality, are listed below:

Body as a Whole: fever, chills, orthostatic effects, facial edema, upper extremity edema

Cardiovascular: flushing, hypertension, cardiac murmur, myocardial infarction, angina pectoris, hypotension, syncope, arrhythmic/conduction disorder, cardiorespiratory arrest, heart failure, hypertensive crisis

Dermatologic: pruritus, dermatitis, ecchymosis, erythema face, urticaria

Endocrine/Metabolic/Electrolyte Imbalances: sexual dysfunction, libido change, gout

Gastrointestinal: diarrhea, constipation, gastroenteritis, flatulence, abdominal distention

Musculoskeletal/Connective Tissue: musculoskeletal trauma, extremity swelling, muscle cramp, arthritis, muscle ache, musculoskeletal chest pain, joint stiffness, bursitis, muscle weakness

Nervous System: anxiety/nervousness, sleep disturbance, numbness, somnolence, vertigo, emotional disturbance, depression, paresthesia, tremor, transient ischemic attack, cerebrovascular accident

Renal/Genitourinary: prostate disorder

Respiratory: cough, upper respiratory infection, epistaxis, tracheobronchitis, congestion, pulmonary congestion, dyspnea, wheezing

Special Senses: vision disturbance, hearing abnormality, ear infection, ear pain, conjunctivitis

Hydrochlorothiazide

Other adverse events that have been reported with hydrochlorothiazide, without regard to causality, are listed below:

Body as a Whole: weakness

Digestive: pancreatitis, jaundice (intrahepatic cholestatic jaundice), sialadenitis, cramping, gastric irritation

Hematologic: aplastic anemia, agranulocytosis, leukopenia, hemolytic anemia, thrombocytopenia

Hypersensitivity: purpura, photosensitivity, urticaria, necrotizing angiitis (vasculitis and cutaneous vasculitis), fever, respiratory distress including pneumonitis and pulmonary edema, anaphylactic reactions

Metabolic: hyperglycemia, glycosuria, hyperuricemia

Musculoskeletal: muscle spasm

Nervous System/Psychiatric: restlessness

Renal: renal failure, renal dysfunction, interstitial nephritis

Skin: erythema multiforme including Stevens-Johnson syndrome, exfoliative dermatitis including toxic epidermal necrolysis

Special Senses: transient blurred vision, xanthopsia

Initial Therapy

In the moderate hypertension Study V (mean SeDBP between 90 and 110 mmHg), the types and incidences of adverse events reported for patients treated with AVALIDE were similar to the adverse event profile in patients on initial irbesartan or HCTZ monotherapy. There were no reported events of syncope in the AVALIDE treatment group and there was one reported event in the HCTZ treatment group. The incidences of prespecified adverse events on AVALIDE, irbesartan, and HCTZ, respectively, were: 0.9%, 0%, and 0% for hypotension; 3.0%, 3.8%, and 1.0% for dizziness; 5.5%, 3.8%, and 4.8% for headache; 1.2%, 0%, and 1.0% for hyperkalemia; and 0.9%, 0%, and 0% for hypokalemia. The rates of discontinuation due to adverse events on AVALIDE, irbesartan alone, and HCTZ alone were 6.7%, 3.8%, and 4.8%.

In the severe hypertension (SeDBP ≥110 mmHg) Study VI, the overall pattern of adverse events reported through 7 weeks of follow-up was similar in patients treated with AVALIDE as initial therapy and in patients treated with irbesartan as initial therapy. The incidences of the prespecified adverse events on AVALIDE and irbesartan, respectively, were: 0% and 0% for syncope; 0.6% and 0% for hypotension; 3.6% and 4.0% for dizziness; 4.3% and 6.6% for headache; 0.2% and 0% for hyperkalemia; and 0.6% and 0.4% for hypokalemia. The rates of discontinuation due to adverse events were 2.1% and 2.2%. [See Clinical Studies (14.2).]

6.2 Postmarketing Experience

The following adverse reactions have been identified during postapproval use of AVALIDE. Because these reactions are reported voluntarily from a population of uncertain size, it is not always possible to reliably estimate their frequency or establish a causal relationship to drug exposure. Decisions to include these reactions in labeling are typically based on one or more of the following factors: (1) seriousness of the reaction, (2) frequency of reporting, or (3) strength of causal connection to AVALIDE.

Irbesartan and hydrochlorothiazide

Blood and lymphatic system: Thrombocytopenia

Hepatobiliary: Hepatitis, Jaundice

Renal and urinary: Impaired renal function including renal failure

Skin and subcutaneous tissue: Urticaria

Irbesartan

Blood and lymphatic system: Anemia

Ear and labyrinth: Tinnitus

Gastrointestinal: Intestinal angioedema

Skin and subcutaneous tissue: Angioedema (involving swelling of the face, lips, pharynx, and/or tongue)

Immune system: Anaphylactic reaction including anaphylactic shock

Investigations: Increased CPK (Creatine Phosphokinase)

Metabolism and nutrition: Hyperkalemia, Hypoglycemia in diabetic patients

Hydrochlorothiazide

Eye: Acute angle-closure glaucoma, Acute myopia, and Choroidal effusion

Non-melanoma Skin Cancer

Hydrochlorothiazide is associated with an increased risk of non-melanoma skin cancer. In a study conducted in the Sentinel System, increased risk was predominantly for squamous cell carcinoma (SCC) and in white patients taking large cumulative doses. The increased risk for SCC in the overall population was approximately 1 additional case per 16,000 patients per year, and for white patients taking a cumulative dose of ≥50,000 mg the risk increase was approximately 1 additional SCC case for every 6,700 patients per year.

6.3 Laboratory Abnormalities

In controlled clinical trials, clinically important changes in standard laboratory parameters were rarely associated with administration of AVALIDE.

Creatinine, Blood Urea Nitrogen: Minor increases in blood urea nitrogen (BUN) or serum creatinine were observed in 2.3% and 1.1%, respectively, of patients with essential hypertension treated with AVALIDE alone. No patient discontinued taking AVALIDE due to increased BUN. One patient discontinued taking AVALIDE due to a minor increase in serum creatinine.

Liver Function Tests: Occasional elevations of liver enzymes and/or serum bilirubin have occurred. In patients with essential hypertension treated with AVALIDE alone, one patient was discontinued due to elevated liver enzymes.

Serum Electrolytes: [See Warnings and Precautions (5.2, 5.6).]

7 DRUG INTERACTIONS

7.1 Nonsteroidal Anti-inflammatory Agents Including Selective Cyclooxygenase-2 Inhibitors (COX-2 Inhibitors)

Irbesartan

In patients who are elderly, volume depleted (including those on diuretic therapy), or with compromised renal function, coadministration of NSAIDs, including selective COX-2 inhibitors, with angiotensin II receptor antagonists, including irbesartan, may result in deterioration of renal function, including possible acute renal failure. These effects are usually reversible. Therefore, monitor renal function and blood pressure periodically in patients receiving irbesartan and NSAID therapy.

Hydrochlorothiazide

Administration of a nonsteroidal anti-inflammatory agent, including a selective COX-2 inhibitor can reduce the diuretic, natriuretic, and antihypertensive effects of loop, potassium-sparing, and thiazide diuretics. Therefore, when AVALIDE (irbesartan and hydrochlorothiazide) tablets and nonsteroidal anti-inflammatory agents are used concomitantly, the patient should be observed closely to determine if the desired effect of the diuretic is obtained.

7.2 Dual Blockade of the Renin-Angiotensin System (RAS)

Dual blockade of the RAS with angiotensin-receptor blockers, ACE inhibitors, or aliskiren is associated with increased risks of hypotension, hyperkalemia, and changes in renal function (including acute renal failure) compared to monotherapy. Closely monitor blood pressure, renal function, and electrolytes in patients on AVALIDE and other agents that affect the RAS.

In most patients no benefit has been associated with using two RAS inhibitors concomitantly. In general, avoid combined use of RAS inhibitors.

Do not coadminister aliskiren with AVALIDE in patients with diabetes. Avoid use of aliskiren with AVALIDE in patients with renal impairment (GFR <60 mL/min).

7.3 Agents Increasing Serum Potassium

Coadministration of AVALIDE with other drugs that raise serum potassium levels may result in hyperkalemia, sometimes severe. Monitor serum potassium in such patients.

7.4 Antidiabetic Drugs (oral agents and insulin)

Dosage adjustment of the antidiabetic drug may be required when coadministered with hydrochlorothiazide.

7.5 Cholestyramine and Colestipol Resins

Absorption of hydrochlorothiazide is impaired in the presence of anionic exchange resins. Stagger the dosage of hydrochlorothiazide and the resin such that AVALIDE is administered at least 4 hours before or 4 to 6 hours after the administration of the resin.

7.6 Lithium

Increases in serum lithium concentrations and lithium toxicity have been reported with concomitant use of irbesartan or thiazide diuretics. Monitor lithium levels in patients receiving AVALIDE and lithium.

7.7 Carbamazepine

Concomitant use of carbamazepine and hydrochlorothiazide has been associated with the risk of symptomatic hyponatremia. Monitor electrolytes during concomitant use.

8 USE IN SPECIFIC POPULATIONS

8.1 Pregnancy

Risk Summary

AVALIDE can cause fetal harm when administered to a pregnant woman. Use of drugs that act on the renin-angiotensin system during the second and third trimesters of pregnancy reduces fetal renal function and increases fetal and neonatal morbidity and death [see Clinical Considerations]. Most epidemiologic studies examining fetal abnormalities after exposure to antihypertensive use in the first trimester have not distinguished drugs affecting the renin-angiotensin system from other antihypertensive agents. When pregnancy is detected, discontinue AVALIDE as soon as possible.

All pregnancies have a background risk of birth defect, loss, or other adverse outcomes regardless of drug exposure. In the U.S. general population, the estimated background risk of major birth defects and miscarriage in clinically recognized pregnancies is 2% to 4% and 15% to 20%, respectively.

Clinical Considerations

Disease-associated maternal and/or embryo-fetal risk

Hypertension in pregnancy increases the maternal risk for preeclampsia, gestational diabetes, premature delivery, and delivery complications (e.g., need for cesarean section and postpartum hemorrhage). Hypertension increases the fetal risk for intrauterine growth restriction and intrauterine death. Pregnant women with hypertension should be carefully monitored and managed accordingly.

Fetal/neonatal adverse reactions

Oligohydramnios in pregnant women who use drugs affecting the renin-angiotensin system in the second and third trimesters of pregnancy can result in the following: reduced fetal renal function leading to anuria and renal failure, fetal lung hypoplasia, skeletal deformations, including skull hypoplasia, hypotension, and death. Perform serial ultrasound examinations to assess the intra-amniotic environment. Fetal testing may be appropriate, based on the week of pregnancy. Patients and physicians should be aware, however, that oligohydramnios may not appear until after the fetus has sustained irreversible injury. Closely observe infants with histories of in utero exposure to AVALIDE for hypotension, oliguria, and hyperkalemia and other symptoms of renal impairment. In neonates with a history of in utero exposure to AVALIDE, if oliguria or hypotension occurs, direct attention toward support of blood pressure and renal perfusion. Exchange transfusion or dialysis may be required as means of reversing hypotension and/or substituting for disordered renal function.

Thiazides cross the placenta, and use of thiazides during pregnancy is associated with a risk of fetal or neonatal jaundice, thrombocytopenia, and possibly other adverse reactions that have occurred in adults [see Warnings and Precautions (5.1)].

Data

Animal data

Irbesartan crosses the placenta in rats and rabbits. In female rats given irbesartan prior to mating through gestation and lactation at oral doses of 50, 180, or 650 mg/kg/day (1.6 to 21.1 times the maximum recommended human dose (MRHD) based on body surface area), fetuses examined on Gestation Day 20 showed increased incidences of hydroureter and renal pelvic cavitation and/or absence of renal papilla in all irbesartan-treated groups. Subcutaneous edema also occurred in fetuses at maternal doses ≥180 mg/kg/day (5.8 times the MRHD). These anomalies occurred when female rats received irbesartan from prior to mating through Day 20 of gestation but were not observed in pups postnatally in the same study, or when irbesartan was given to pregnant rats only during organogenesis (Gestation Day 6 through Gestation Day 15) at oral doses from 50 to 450 mg/kg/day (up to 14.6 times the MRHD). In addition, no adverse effects on kidney development were observed in pups from dams given irbesartan from Gestation Day 15 through Lactation Day 24 at doses of 50, 180, or 650 mg/kg/day (up to 21.1 times the MRHD). The observed effects are believed to be late gestational effects of the drug. Pregnant rabbits given oral doses of irbesartan of 30 mg/kg/day (1.9 times the MRHD based on body surface area) experienced a high rate of maternal mortality and abortion. Surviving females had a slight increase in early resorptions and a corresponding decrease in live fetuses.

Radioactivity was present in the rat and rabbit fetuses during late gestation following oral doses of radiolabeled irbesartan.

When pregnant mice and rats were given hydrochlorothiazide at doses up to 3000 and 1000 mg/kg/day, respectively (about 600 and 400 times the MRHD) during their respective periods of major organogenesis, there was no evidence of fetal harm.

A development toxicity study was performed in rats with doses of 50/50 mg/kg/day and 150/150 mg/kg/day irbesartan and hydrochlorothiazide. Although the high dose combination appeared to be more toxic to the dams than either drug alone, there did not appear to be an increase in toxicity to the developing embryos.

8.2 Lactation

There are no available data on the presence of irbesartan in human milk, effects on milk production, or the breastfed infant. Irbesartan or some metabolite of irbesartan is secreted in the milk of lactating rats. Thiazides appear in human milk [see Clinical Pharmacology (12.3)]. Because of the potential for adverse effects on the nursing infant, the use of AVALIDE in breastfeeding women is not recommended.

8.4 Pediatric Use

Safety and effectiveness in pediatric patients have not been established.

8.5 Geriatric Use

Of 1694 patients receiving AVALIDE in controlled clinical studies of hypertension, 264 (15.6%) were 65 years and over, while 45 (2.7%) were 75 years and over. No overall differences in safety or effectiveness were observed between these patients and younger patients, but greater sensitivity of some older individuals cannot be ruled out. [See Clinical Pharmacology (12.3) and Clinical Studies (14).]

10 OVERDOSAGE

Irbesartan

No data are available in regard to overdosage in humans. However, daily doses of 900 mg for 8 weeks were well tolerated. The most likely manifestations of overdosage are expected to be hypotension and tachycardia; bradycardia might also occur from overdose. Irbesartan is not removed by hemodialysis.

To obtain up-to-date information about the treatment of overdosage, a good resource is a certified regional Poison Control Center. Telephone numbers of certified Poison Control Centers are listed in the Physicians' Desk Reference (PDR). In managing overdose, consider the possibilities of multiple-drug interactions, drug-drug interactions, and unusual drug kinetics in the patient.

Laboratory determinations of serum levels of irbesartan are not widely available, and such determinations have, in any event, no established role in the management of irbesartan overdose.

Acute oral toxicity studies with irbesartan in mice and rats indicated acute lethal doses were in excess of 2000 mg/kg, about 25-fold and 50-fold the MRHD (300 mg) based on body surface area.

Hydrochlorothiazide

The most common signs and symptoms of overdose observed in humans are those caused by electrolyte depletion (hypokalemia, hypochloremia, hyponatremia) and dehydration resulting from excessive diuresis. If digitalis has also been administered, hypokalemia may accentuate cardiac arrhythmias. The degree to which hydrochlorothiazide is removed by hemodialysis has not been established. The oral LD50 of hydrochlorothiazide is greater than 10 g/kg in both mice and rats.

11 DESCRIPTION

AVALIDE (irbesartan and hydrochlorothiazide) tablets are a combination of an angiotensin II receptor antagonist (AT1 subtype), irbesartan, and a thiazide diuretic, hydrochlorothiazide (HCTZ).

Irbesartan is a non-peptide compound, chemically described as a 2-butyl-3-[p-(o-1H-tetrazol-5-ylphenyl) benzyl]-1,3-diazaspiro[4.4]non-1-en-4-one. Its empirical formula is C25H28N6O, and its structural formula is:

Irbesartan is a white to off-white crystalline powder with a molecular weight of 428.5. It is a nonpolar compound with a partition coefficient (octanol/water) of 10.1 at pH of 7.4. Irbesartan is slightly soluble in alcohol and methylene chloride and practically insoluble in water.

Hydrochlorothiazide is 6-chloro-3,4-dihydro-2H-1,2,4-benzothiadiazine-7-sulfonamide 1,1-dioxide. Its empirical formula is C7H8ClN3O4S2 and its structural formula is:

Hydrochlorothiazide is a white, or practically white, crystalline powder with a molecular weight of 297.7. Hydrochlorothiazide is slightly soluble in water and freely soluble in sodium hydroxide solution.

AVALIDE is available for oral administration in film-coated tablets containing either 150 mg or 300 mg of irbesartan combined with 12.5 mg of hydrochlorothiazide. All dosage strengths contain the following inactive ingredients: lactose monohydrate, microcrystalline cellulose, croscarmellose sodium, hypromellose, magnesium stearate, silicon dioxide, ferric oxide red, ferric oxide yellow, polyethylene glycol, titanium dioxide, and carnauba wax.

12 CLINICAL PHARMACOLOGY

12.1 Mechanism of Action

Irbesartan

Angiotensin II is a potent vasoconstrictor formed from angiotensin I in a reaction catalyzed by angiotensin-converting enzyme (ACE, kininase II). Angiotensin II is the principal pressor agent of the RAS and also stimulates aldosterone synthesis and secretion by adrenal cortex, cardiac contraction, renal resorption of sodium, activity of the sympathetic nervous system, and smooth muscle cell growth. Irbesartan blocks the vasoconstrictor and aldosterone-secreting effects of angiotensin II by selectively binding to the AT1 angiotensin II receptor. There is also an AT2 receptor in many tissues, but it is not involved in cardiovascular homeostasis.

Irbesartan is a specific competitive antagonist of AT1 receptors with a much greater affinity (more than 8500-fold) for the AT1 receptor than for the AT2 receptor, and no agonist activity.

Blockade of the AT1 receptor removes the negative feedback of angiotensin II on renin secretion, but the resulting increased plasma renin activity and circulating angiotensin II do not overcome the effects of irbesartan on blood pressure.

Irbesartan does not inhibit ACE or renin or affect other hormone receptors or ion channels known to be involved in the cardiovascular regulation of blood pressure and sodium homeostasis. Because irbesartan does not inhibit ACE, it does not affect the response to bradykinin; whether this has clinical relevance is not known.

Hydrochlorothiazide

Hydrochlorothiazide is a thiazide diuretic. Thiazides affect the renal tubular mechanisms of electrolyte reabsorption, directly increasing excretion of sodium and chloride in approximately equivalent amounts. Indirectly, the diuretic action of hydrochlorothiazide reduces plasma volume, with consequent increases in plasma renin activity, increases in aldosterone secretion, increases in urinary potassium loss, and decreases in serum potassium. The renin-aldosterone link is mediated by angiotensin II, so coadministration of an angiotensin II receptor antagonist tends to reverse the potassium loss associated with these diuretics.

The mechanism of the antihypertensive effect of thiazides is not fully understood.

12.2 Pharmacodynamics

Irbesartan

In healthy subjects, single oral irbesartan doses of up to 300 mg produced dose-dependent inhibition of the pressor effect of angiotensin II infusions. Inhibition was complete (100%) 4 hours following oral doses of 150 mg or 300 mg and partial inhibition was sustained for 24 hours (60% and 40% at 300 mg and 150 mg, respectively).

In hypertensive patients, angiotensin II receptor inhibition following chronic administration of irbesartan causes a 1.5-fold to 2-fold rise in angiotensin II plasma concentration and a 2-fold to 3-fold increase in plasma renin levels. Aldosterone plasma concentrations generally decline following irbesartan administration, but serum potassium levels are not significantly affected at recommended doses.

In hypertensive patients, chronic oral doses of irbesartan (up to 300 mg) had no effect on glomerular filtration rate, renal plasma flow or filtration fraction. In multiple dose studies in hypertensive patients, there were no clinically important effects on fasting triglycerides, total cholesterol, HDL-cholesterol, or fasting glucose concentrations. There was no effect on serum uric acid during chronic oral administration and no uricosuric effect.

Hydrochlorothiazide

After oral administration of hydrochlorothiazide, diuresis begins within 2 hours, peaks in about 4 hours and lasts about 6 to 12 hours.

Drug Interactions

Hydrochlorothiazide

Alcohol, barbiturates, or narcotics: Potentiation of orthostatic hypotension may occur.

Skeletal muscle relaxants: Possible increased responsiveness to muscle relaxants such as curare derivatives.

Corticosteroids, ACTH: Intensified electrolyte depletion, particularly hypokalemia.

Pressor amines (e.g., norepinephrine): Possible decreased response to pressor amines but not sufficient to preclude their use.

12.3 Pharmacokinetics

Irbesartan

Irbesartan is an orally active agent that does not require biotransformation into an active form. The oral absorption of irbesartan is rapid and complete with an average absolute bioavailability of 60% to 80%. Following oral administration of irbesartan, peak plasma concentrations of irbesartan are attained at 1.5 to 2 hours after dosing. Food does not affect the bioavailability of irbesartan.

Irbesartan exhibits linear pharmacokinetics over the therapeutic dose range.

The terminal elimination half-life of irbesartan averaged 11 to 15 hours. Steady-state concentrations are achieved within 3 days. Limited accumulation of irbesartan (<20%) is observed in plasma upon repeated once-daily dosing.

Hydrochlorothiazide

When plasma levels have been followed for at least 24 hours, the plasma half-life has been observed to vary between 5.6 and 14.8 hours.

Metabolism and Elimination

Irbesartan

Irbesartan is metabolized via glucuronide conjugation and oxidation. Following oral or intravenous administration of ^14C-labeled irbesartan, more than 80% of the circulating plasma radioactivity is attributable to unchanged irbesartan. The primary circulating metabolite is the inactive irbesartan glucuronide conjugate (approximately 6%). The remaining oxidative metabolites do not add appreciably to irbesartan's pharmacologic activity.

Irbesartan and its metabolites are excreted by both biliary and renal routes. Following either oral or intravenous administration of ^14C-labeled irbesartan, about 20% of radioactivity is recovered in the urine and the remainder in the feces, as irbesartan or irbesartan glucuronide.

In vitro studies of irbesartan oxidation by cytochrome P450 isoenzymes indicated irbesartan was oxidized primarily by 2C9; metabolism by 3A4 was negligible. Irbesartan was neither metabolized by, nor did it substantially induce or inhibit, isoenzymes commonly associated with drug metabolism (1A1, 1A2, 2A6, 2B6, 2D6, 2E1). There was no induction or inhibition of 3A4.

Hydrochlorothiazide

Hydrochlorothiazide is not metabolized but is eliminated rapidly by the kidney. At least 61% of the oral dose is eliminated unchanged within 24 hours.

Distribution

Irbesartan

Irbesartan is 90% bound to serum proteins (primarily albumin and α1-acid glycoprotein) with negligible binding to cellular components of blood. The average volume of distribution is 53 to 93 liters. Total plasma and renal clearances are in the range of 157 to 176 mL/min and 3.0 to 3.5 mL/min, respectively. With repetitive dosing, irbesartan accumulates to no clinically relevant extent.

Studies in animals indicate that radiolabeled irbesartan weakly crosses the blood-brain barrier and placenta. Irbesartan is excreted in the milk of lactating rats.

Hydrochlorothiazide

Hydrochlorothiazide crosses the placental but not the blood-brain barrier and is excreted in breast milk.

Specific Populations

Pediatric

Irbesartan and hydrochlorothiazide pharmacokinetics have not been investigated in patients <18 years of age.

Gender

No gender-related differences in pharmacokinetics were observed in healthy elderly (age 65 to 80 years) or in healthy young (age 18 to 40 years) subjects. In studies of hypertensive patients, there was no gender difference in half-life or accumulation, but somewhat higher plasma concentrations of irbesartan were observed in females (11% to 44%). No gender-related dosage adjustment is necessary.

Geriatric

In elderly subjects (age 65 to 80 years), irbesartan elimination half-life was not significantly altered, but AUC and Cmax values were about 20% to 50% greater than those of young subjects (age 18 to 40 years). No dosage adjustment is necessary in the elderly.

Race

In healthy black subjects, irbesartan AUC values were approximately 25% greater than whites; there were no differences in Cmax values.

Renal insufficiency

The pharmacokinetics of irbesartan were not altered in patients with renal impairment or in patients on hemodialysis. Irbesartan is not removed by hemodialysis. No dosage adjustment is necessary in patients with mild to severe renal impairment unless a patient with renal impairment is also volume depleted. [See Warnings and Precautions (5.2).]

Hepatic insufficiency

The pharmacokinetics of irbesartan following repeated oral administration were not significantly affected in patients with mild to moderate cirrhosis of the liver. No dosage adjustment is necessary in patients with hepatic insufficiency.

Drug-Drug Interactions

No significant drug-drug pharmacokinetic (or pharmacodynamic) interactions have been found in interaction studies with hydrochlorothiazide, digoxin, warfarin, and nifedipine.

In vitro studies show significant inhibition of the formation of oxidized irbesartan metabolites with the known cytochrome CYP2C9 substrates/inhibitors sulphenazole, tolbutamide, and nifedipine. However, in clinical studies the consequences of concomitant irbesartan on the pharmacodynamics of warfarin were negligible. Concomitant nifedipine or hydrochlorothiazide had no effect on irbesartan pharmacokinetics. Based on in vitro data, no interaction would be expected with drugs whose metabolism is dependent upon cytochrome P450 isoenzymes 1A1, 1A2, 2A6, 2B6, 2D6, 2E1, or 3A4.

In separate studies of patients receiving maintenance doses of warfarin, hydrochlorothiazide, or digoxin, irbesartan administration for 7 days had no effect on the pharmacodynamics of warfarin (prothrombin time) or the pharmacokinetics of digoxin. The pharmacokinetics of irbesartan were not affected by coadministration of nifedipine or hydrochlorothiazide.

13 NONCLINICAL TOXICOLOGY

13.1 Carcinogenesis, Mutagenesis, Impairment of Fertility

Irbesartan and Hydrochlorothiazide

No carcinogenicity studies have been conducted with the irbesartan and hydrochlorothiazide combination.

Irbesartan and hydrochlorothiazide was not mutagenic in standard in vitro tests (Ames microbial test and Chinese hamster mammalian-cell forward gene-mutation assay). Irbesartan and hydrochlorothiazide was negative in tests for induction of chromosomal aberrations (in vitro–human lymphocyte assay; in vivo–mouse micronucleus study).

The combination of irbesartan and hydrochlorothiazide has not been evaluated in definitive studies of fertility.

Irbesartan

No evidence of carcinogenicity was observed when irbesartan was administered at doses of up to 500/1000 mg/kg/day (males/females, respectively) in rats and 1000 mg/kg/day in mice for up to 2 years. For male and female rats, 500 mg/kg/day provided an average systemic exposure to irbesartan (AUC0–24 hours, bound plus unbound) about 3 and 11 times, respectively, the average systemic exposure in humans receiving the maximum recommended human dose (MRHD) of 300 mg irbesartan/day, whereas 1000 mg/kg/day (administered to females only) provided an average systemic exposure about 21 times that reported for humans at the MRHD. For male and female mice, 1000 mg/kg/day provided an exposure to irbesartan about 3 and 5 times, respectively, the human exposure at 300 mg/day.

Irbesartan was not mutagenic in a battery of in vitro tests (Ames microbial test, rat hepatocyte DNA repair test, V79 mammalian-cell forward gene-mutation assay). Irbesartan was negative in several tests for induction of chromosomal aberrations (in vitro–human lymphocyte assay; in vivo–mouse micronucleus study).

Irbesartan had no adverse effects on fertility or mating of male or female rats at oral doses ≤650 mg/kg/day, the highest dose providing a systemic exposure to irbesartan (AUC0–24 hours, bound plus unbound) about 5 times that found in humans receiving the MRHD of 300 mg/day.

Hydrochlorothiazide

Two-year feeding studies in mice and rats conducted under the auspices of the National Toxicology Program (NTP) uncovered no evidence of a carcinogenic potential of hydrochlorothiazide in female mice (at doses of up to approximately 600 mg/kg/day) or in male and female rats (at doses of up to approximately 100 mg/kg/day). The NTP, however, found equivocal evidence for hepatocarcinogenicity in male mice.

Hydrochlorothiazide was not genotoxic in vitro in the Ames mutagenicity assay of Salmonella typhimurium strains TA 98, TA 100, TA 1535, TA 1537, and TA 1538 and in the Chinese Hamster Ovary (CHO) test for chromosomal aberrations, or in vivo in assays using mouse germinal cell chromosomes, Chinese hamster bone marrow chromosomes, and the Drosophila sex-linked recessive lethal trait gene. Positive test results were obtained only in the in vitro CHO Sister Chromatid Exchange (clastogenicity) and in the Mouse Lymphoma Cell (mutagenicity) assays, using concentrations of hydrochlorothiazide from 43 to 1300 µg/mL, and in the Aspergillus nidulans non-disjunction assay at an unspecified concentration.

Hydrochlorothiazide had no adverse effects on the fertility of mice and rats of either sex in studies wherein these species were exposed, via their diet, to doses of up to 100 and 4 mg/kg, respectively, prior to mating and throughout gestation.

14 CLINICAL STUDIES

14.1 Irbesartan Monotherapy

The antihypertensive effects of irbesartan were examined in 7 major placebo-controlled, 8 to 12-week trials in patients with baseline diastolic blood pressures of 95 to 110 mmHg. Doses of 1 to 900 mg were included in these trials in order to fully explore the dose-range of irbesartan. These studies allowed a comparison of once or twice-daily regimens at 150 mg/day, comparisons of peak and trough effects, and comparisons of response by gender, age, and race. Two of the 7 placebo-controlled trials identified above and 2 additional placebo-controlled studies examined the antihypertensive effects of irbesartan and hydrochlorothiazide in combination.

The 7 studies of irbesartan monotherapy included a total of 1915 patients randomized to irbesartan (1 to 900 mg) and 611 patients randomized to placebo. Once-daily doses of 150 to 300 mg provided statistically and clinically significant decreases in systolic and diastolic blood pressure with trough (24-hour post dose) effects after 6 to 12 weeks of treatment compared to placebo, of about 8 to 10/5 to 6 mmHg and 8 to 12/5 to 8 mmHg, respectively. No further increase in effect was seen at dosages greater than 300 mg. The dose-response relationships for effects on systolic and diastolic pressure are shown in Figures 3 and 4.

Once-daily administration of therapeutic doses of irbesartan gave peak effects at around 3 to 6 hours and, in one continuous ambulatory blood pressure monitoring study, again around 14 hours. This was seen with both once-daily and twice-daily dosing. Trough-to-peak ratios for systolic and diastolic response were generally between 60% and 70%. In a continuous ambulatory blood pressure monitoring study, once-daily dosing with 150 mg gave trough and mean 24-hour responses similar to those observed in patients receiving twice-daily dosing at the same total daily dose.

Analysis of age, gender, and race subgroups of patients showed that men and women, and patients over and under 65 years of age, had generally similar responses. Irbesartan was effective in reducing blood pressure regardless of race, although the effect was somewhat less in blacks (usually a low-renin population). Black patients typically show an improved response with the addition of a low dose diuretic (e.g., 12.5 mg hydrochlorothiazide).

The effect of irbesartan is apparent after the first dose and is close to the full observed effect at 2 weeks. At the end of the 8-week exposure, about 2/3 of the antihypertensive effect was still present 1 week after the last dose. Rebound hypertension was not observed. There was essentially no change in average heart rate in irbesartan-treated patients in controlled trials.

14.2 Irbesartan and Hydrochlorothiazide

The antihypertensive effects of AVALIDE (irbesartan and hydrochlorothiazide) tablets were examined in 4 placebo-controlled studies in patients with mild-moderate hypertension (mean seated diastolic blood pressure [SeDBP] between 90 and 110 mmHg), one study in patients with moderate hypertension (mean seated systolic blood pressure [SeSBP] 160 to 179 mmHg or SeDBP 100 to 109 mmHg), and one study in patients with severe hypertension (mean SeDBP ≥110 mmHg) of 8 to 12 weeks. These trials included 3149 patients randomized to fixed doses of irbesartan (37.5 to 300 mg) and concomitant hydrochlorothiazide (6.25 to 25 mg).

Study I was a factorial study that compared all combinations of irbesartan (37.5 mg, 100 mg, and 300 mg or placebo) and hydrochlorothiazide (6.25 mg, 12.5 mg, and 25 mg or placebo).

Study II compared the irbesartan and hydrochlorothiazide combinations of 75/12.5 mg and 150/12.5 mg to their individual components and placebo.

Study III investigated the ambulatory blood pressure responses to irbesartan and hydrochlorothiazide (75/12.5 mg and 150/12.5 mg) and placebo after 8 weeks of dosing.

Study IV investigated the effects of the addition of irbesartan (75 or 150 mg) in patients not controlled (SeDBP 93–120 mmHg) on hydrochlorothiazide (25 mg) alone. In Studies I–III, the addition of irbesartan 150 to 300 mg to hydrochlorothiazide doses of 6.25, 12.5, or 25 mg produced further dose-related reductions in blood pressure at trough of 8 to 10 mmHg/3 to 6 mmHg, similar to those achieved with the same monotherapy dose of irbesartan. The addition of hydrochlorothiazide to irbesartan produced further dose-related reductions in blood pressure at trough (24 hours post dose) of 5 to 6/2 to 3 mmHg (12.5 mg) and 7 to 11/4 to 5 mmHg (25 mg), also similar to effects achieved with hydrochlorothiazide alone. Once-daily dosing with 150 mg irbesartan and 12.5 mg hydrochlorothiazide, 300 mg irbesartan and 12.5 mg hydrochlorothiazide, or 300 mg irbesartan and 25 mg hydrochlorothiazide produced mean placebo-adjusted blood pressure reductions at trough (24 hours post dosing) of about 13 to 15/7 to 9 mmHg, 14/9 to 12 mmHg, and 19 to 21/11 to 12 mmHg, respectively. Peak effects occurred at 3 to 6 hours, with the trough-to-peak ratios >65%.

In Study IV, the addition of irbesartan (75–150 mg) gave an additive effect (systolic/diastolic) at trough (24 hours post dosing) of 11/7 mmHg.

Initial Therapy

Studies V and VI had no placebo group, so effects described below are not all attributable to irbesartan or HCTZ.

Study V was conducted in patients with a mean baseline blood pressure of 162/98 mmHg and compared the change from baseline in SeSBP at 8 weeks between the combination group (irbesartan and HCTZ 150/12.5 mg), to irbesartan (150 mg) and to HCTZ (12.5 mg). These initial study regimens were increased at 2 weeks to AVALIDE 300/25 mg, irbesartan 300 mg, or to HCTZ 25 mg, respectively.

Mean reductions from baseline for SeDBP and SeSBP at trough were 14.6 mmHg and 27.1 mmHg for patients treated with AVALIDE, 11.6 mmHg and 22.1 mmHg for patients treated with irbesartan, and 7.3 mmHg and 15.7 mmHg for patients treated with HCTZ at 8 weeks, respectively. For patients treated with AVALIDE, the mean change from baseline in SeDBP was 3.0 mmHg lower (p=0.0013) and the mean change from baseline in SeSBP was 5.0 mmHg lower (p=0.0016) compared to patients treated with irbesartan, and 7.4 mmHg lower (p<0.0001) and 11.3 mmHg lower (p<0.0001) compared to patients treated with HCTZ, respectively. Withdrawal rates were 3.8% on irbesartan, 4.8% on HCTZ, and 6.7% on AVALIDE.

Study VI was conducted in patients with a mean baseline blood pressure of 172/113 mmHg and compared trough SeDBP at 5 weeks between the combination group (irbesartan and HCTZ 150/12.5 mg) and irbesartan (150 mg). These initial study regimens were increased at 1 week to AVALIDE 300/25 mg or to irbesartan 300 mg, respectively.

At 5 weeks, mean reductions from baseline for SeDBP and SeSBP at trough were 24.0 mmHg and 30.8 mmHg for patients treated with AVALIDE and 19.3 mmHg and 21.1 mmHg for patients treated with irbesartan, respectively. The mean SeDBP was 4.7 mmHg lower (p<0.0001) and the mean SeSBP was 9.7 mmHg lower (p<0.0001) in the group treated with AVALIDE than in the group treated with irbesartan. Patients treated with AVALIDE achieved more rapid blood pressure control with significantly lower SeDBP and SeSBP and greater blood pressure control at every assessment (Week 1, Week 3, Week 5, and Week 7). Maximum effects were seen at Week 7.

Withdrawal rates were 2.2% on irbesartan and 2.1% on AVALIDE.

In Studies I–VI, there was no difference in response for men and women or in patients over or under 65 years of age. Black patients had a larger response to hydrochlorothiazide than non-black patients and a smaller response to irbesartan. The overall response to the combination was similar for black and non-black patients.

16 HOW SUPPLIED/STORAGE AND HANDLING

16.1 How Supplied

AVALIDE® (irbesartan and hydrochlorothiazide) film-coated tablets have markings on both sides and are available in the strengths and packages listed in the following table:

Tablet Strength (irbesartan and hydrochlorothiazide) | Film-Coated Tablet Color/Shape | Tablet Markings | Package Size | NDC Code
150 mg and 12.5 mg | peach, biconvex, oval-shaped | heart debossed on one side and "2875" on the reverse | Bottles of 30 | 0024-5855-30
300 mg and 12.5 mg | peach, biconvex, oval-shaped | heart debossed on one side and "2876" on the reverse | Bottles of 30 | 0024-5856-30

16.2 Storage

Store at 25°C (77°F); excursions permitted to 15°C–30°C (59°F–86°F) [see USP Controlled Room Temperature].

17 PATIENT COUNSELING INFORMATION

Pregnancy

Tell female patients of childbearing age about the consequences of exposure to AVALIDE during pregnancy. Discuss treatment options with women planning to become pregnant. Ask patients to report pregnancies to their physician as soon as possible.

Symptomatic Hypotension

Tell patients using AVALIDE that they may feel lightheaded, especially during the first days of use. Tell patients to inform their physician if they feel lightheaded or faint. Tell the patient, if fainting occurs, stop using AVALIDE and contact the prescribing doctor.

Tell patients using AVALIDE that getting dehydrated can lower their blood pressure too much and lead to lightheadedness and possible fainting. Dehydration may occur with excessive sweating, diarrhea, or vomiting and with not drinking enough liquids.

Potassium Supplements

Advise patients not to use potassium supplements or salt substitutes containing potassium without consulting their healthcare provider [see Drug Interactions (7.3)].

Acute Angle-Closure Glaucoma, Acute Myopia, and Choroidal Effusion

Advise patients to discontinue AVALIDE and seek immediate medical attention if they experience symptoms of acute angle-closure glaucoma, acute myopia, and choroidal effusion [see Warnings and Precautions (5.8)].

Non-melanoma Skin Cancer

Instruct patients taking hydrochlorothiazide to protect skin from the sun and undergo regular skin cancer screening.

sanofi-aventis U.S. LLC
Morristown, NJ 07960
A SANOFI COMPANY

©2025 sanofi-aventis U.S. LLC

PRINCIPAL DISPLAY PANEL - 150/12.5 mg Tablet Bottle Label

NDC 0024-5855-30
Rx only

Avalide®
(irbesartan and
hydrochlorothiazide)
Tablets
150/12.5 mg

30 Tablets
sanofi

PRINCIPAL DISPLAY PANEL - 300/12.5 mg Tablet Bottle Label

NDC 0024-5856-30
Rx only

Avalide®
(irbesartan and
hydrochlorothiazide)
Tablets
300/12.5 mg

30 Tablets
sanofi